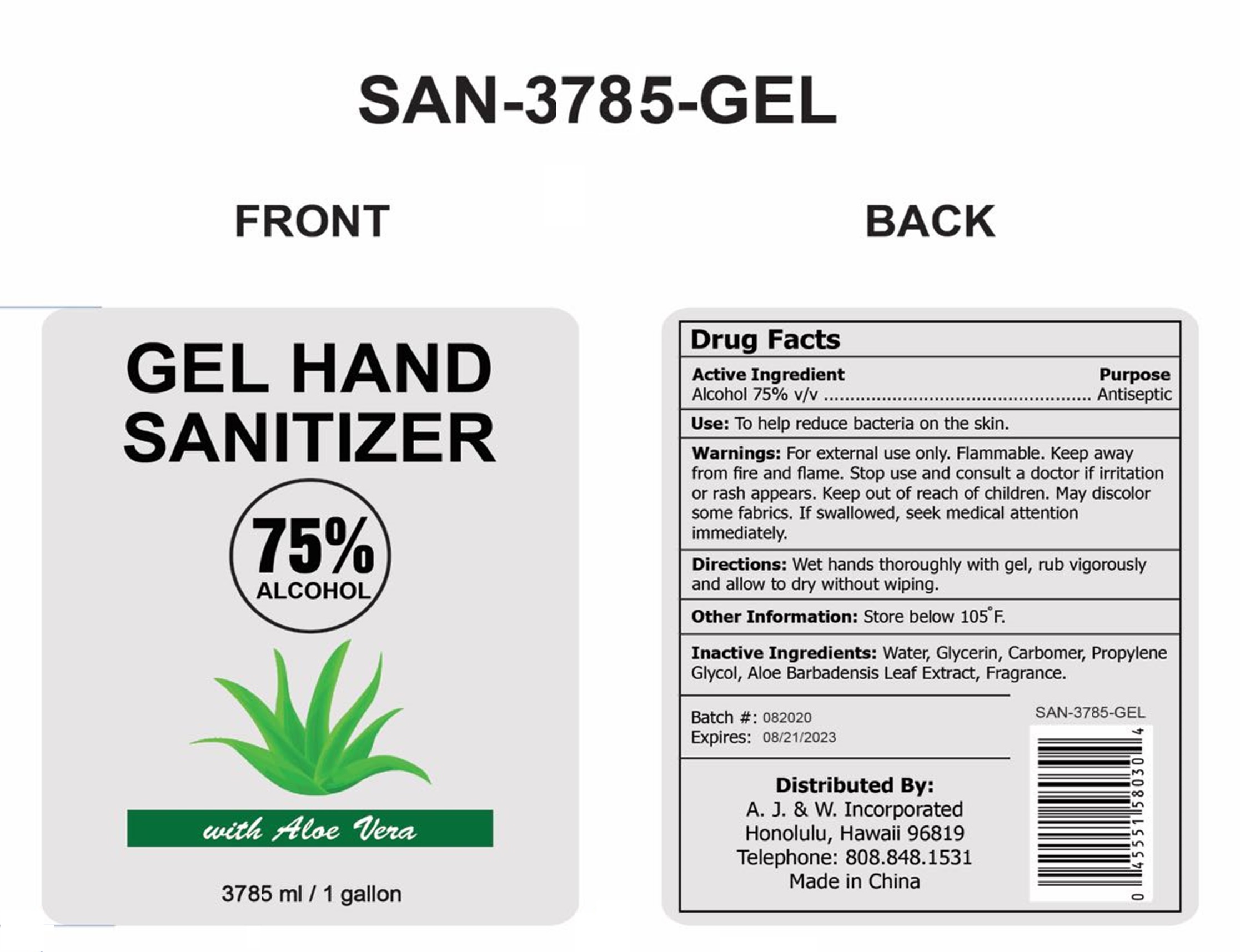 DRUG LABEL: Gel Hand Sanitizer
NDC: 75742-012 | Form: GEL
Manufacturer: Zhejiang Guoyao Jingyue Aerosol Co., Ltd.
Category: otc | Type: HUMAN OTC DRUG LABEL
Date: 20200907

ACTIVE INGREDIENTS: ALCOHOL 75 mL/100 mL
INACTIVE INGREDIENTS: WATER; CARBOMER HOMOPOLYMER, UNSPECIFIED TYPE; GLYCERIN; PROPYLENE GLYCOL; ALOE VERA LEAF

GEL Hand sanitizer with Aloe Vera (1 Gallon)

Active Ingredient

Alcohol 75% v/v

Purpose

Antiseptic

Uses

To help reduce bacteria on the skin.

Warnings

For external use only. Flammable, keep away from fire and flame. May discolor certain fabrics

OTC-STOP USE SECTION

Stop use and consult a doctor if irritation or rash appears.

OTC-KEEP OUT OF REACH OF CHILDREN SECTION

Keep out of reach of children.

OTC-DO NOT USE SECTION

If swallowed, seek medical attention immediately.

Directions

Wet hands thoroughly with gel, rub vigorously and allow to dry without wiping.

Other information

Store below 105°F.

INACTIVE INGREDIENT SECTION

Water, Glycerin, Carbomer, Propylene Glycol, Aloe Barbadensis Leaf Extract, Fragrance